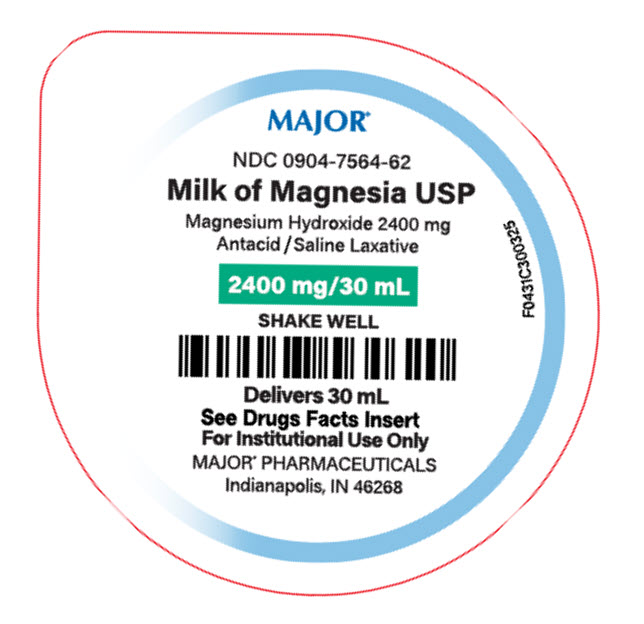 DRUG LABEL: Milk of Magnesia
NDC: 0904-7564 | Form: SUSPENSION
Manufacturer: Major Pharmaceuticals
Category: otc | Type: HUMAN OTC DRUG LABEL
Date: 20260105

ACTIVE INGREDIENTS: MAGNESIUM HYDROXIDE 2400 mg/30 mL
INACTIVE INGREDIENTS: CYCLOMETHICONE 4; HYPROMELLOSE 2910 (4000 MPA.S); METHYLPARABEN; POTASSIUM CITRATE; PROPYLENE GLYCOL; PROPYLPARABEN; WATER; SACCHARIN SODIUM; SORBITOL

Milk of Magnesia

Drug Facts

Active ingredient (in each 30 mL dose)

Magnesium hydroxide 2400 mg

Purpose

Antacid / Saline Laxative

Uses as Antacid

• relieves
• heartburn
• sour stomach
• acid indigestion
• and upset stomach associated with these symptoms

Uses as Saline Laxative

• for relief of occasional constipation (irregularity)
• this product generally produces bowel movement in 1/2 to 6 hours

Warnings for Antacid

Ask a doctor before use if you have

• kidney disease
• a magnesium-restricted diet

Ask a doctor or pharmacist before use If you are presently taking a prescription drug. Antacids may interact with certain prescription drugs.

When using this product

• do not take more than 60 mL (2 doses) in a 24-hour period
• do not use the maximum dosage for more than 2 weeks except under the advice and superision of a doctor
• may cause a laxative effect

PREGNANCY OR BREAST FEEDING

If pregnant or breast-feeding, ask a health professional before use.

Keep out of reach of children. In case of overdose, get medical help or contact a poison control center right away.

Warnings for Saline Laxative

Ask a doctor before use if you have

• kidney disease
• a magnesium-restricted diet
• abdominal pain, nausea, or vomiting
• a sudden change in bowel habits that lasts more than 2 weeks

Ask a doctor or pharmacist before use If you are

• presently taking a prescription drug. This product may interact with certain prescription drugs.

Stop use and ask a doctor if

• you have rectal bleeding or no bowel movement after using this product. These could be signs of a seriouscondition.
• you need to use a laxative for more that 1 week

PREGNANCY OR BREAST FEEDING

If pregnant or breast-feeding,ask a health professional before use.

Keep out of reach of children. In case of overdose, get medical help or contact a Poison Control Center right away.

Directions for Antacid

• shake well before use
• mL=milliliters
• adults and children 12 years of age or older: 30 mL (1 dose) up to 2 times a day or as directed by a doctor
• children under 12 years of age: ask a doctor

Directions for Saline Laxative

• do not exceed the maximum recommended daily dose of 60 mL in a 24 hour period
• shake well before use
• mL=milliliters
• drink a full glass (8 oz) of liquid with each dose
• adults and children 12 years of age or older: 30 mL to 60 mL (1 to 2 doses)
• children under 12 years of age: ask a doctor
• the dose may be taken as a single daily dose or in divided doses

Other information for Antacid

• each 30 mL contains: magnesium 1 g
• store at 20° - 25°C (68° - 77°F)
• protect from freezing
• tamper-evident: do not use if seal on cup is missing or torn

Other information for Saline Laxative

• each 30 mL contains: magnesium 1 g
• store at 20° - 25°C (68° - 77°F)
• protect from freezing
• tamper-evident: do not use if seal on cup is missing or torn

INACTIVE INGREDIENT

Inactive ingredients antifoam af emulsion, flavoring, hydroxypropyl methylcellulose, methylparaben, potassium citrate, propylene glycol, propylparaben, purified water, sodium saccharin, sorbitol

Questions or comments? call 1-800-845-8210

R03/25
Distributed by:
MAJOR® PHARMACEUTICALS
Indianapolis, IN 46268

PRINCIPAL DISPLAY PANEL - 30 mL Cup Tray Label

MAJOR®

NDC 0904-7564-62

Milk of Magnesia USP
Magnesium Hydroxide 2400 mg
Antacid / Saline Laxative

2400 mg/ 30 mL

SHAKE WELL

Delivers 30 mL
See Drugs Facts Insert
For Institutional Use Only

MAJOR® PHARMACEUTICALS
Indianapolis, IN 46268

F0431C300325